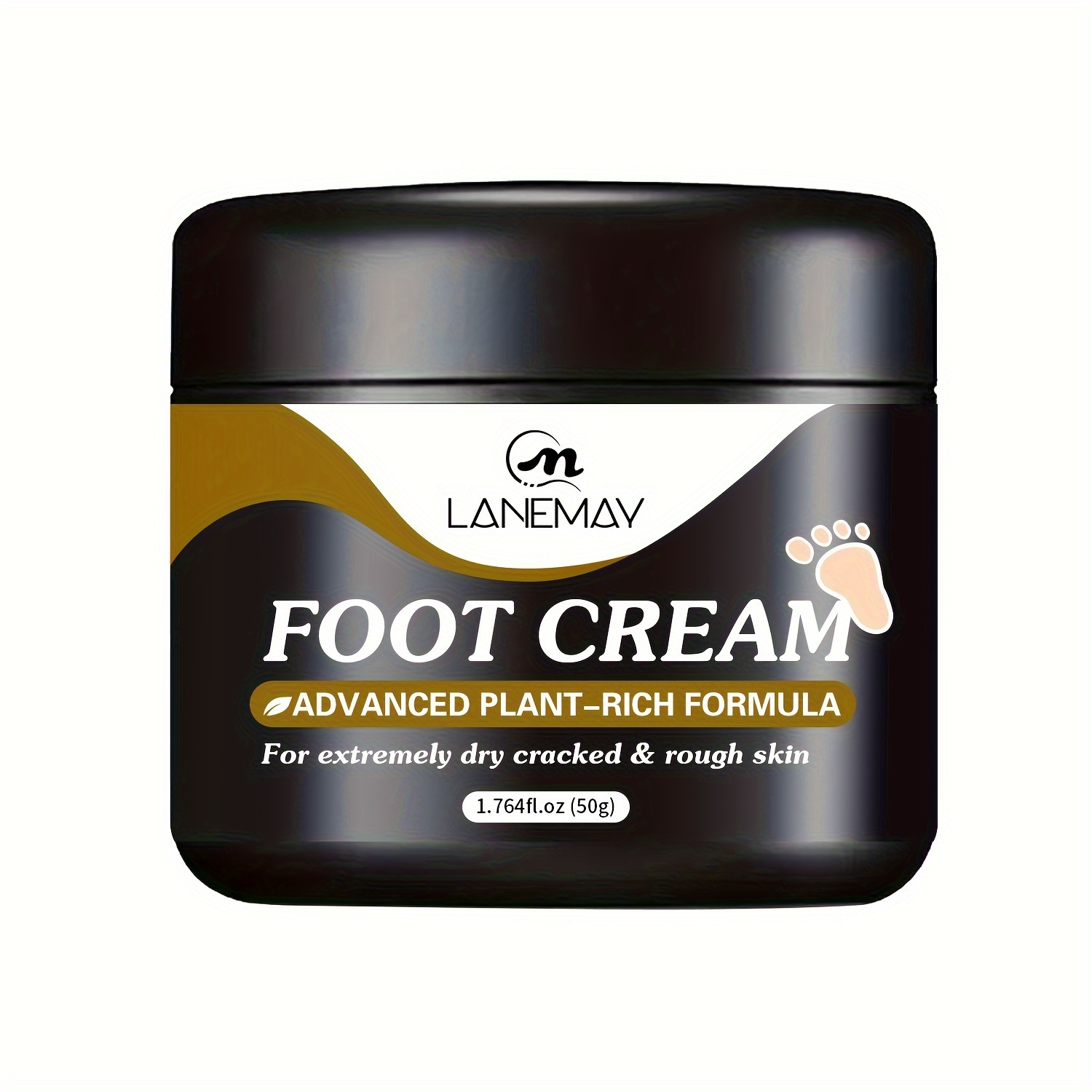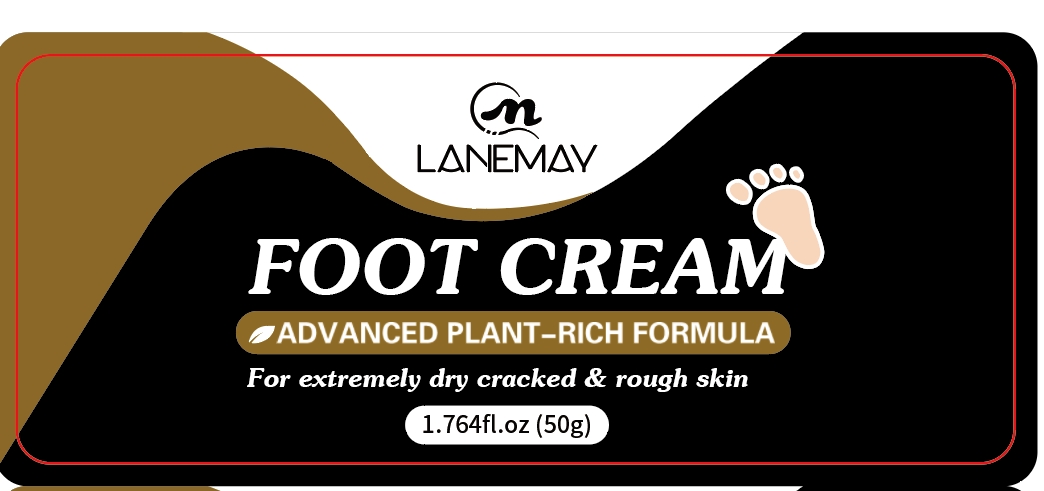 DRUG LABEL: Foot Cream
NDC: 84025-041 | Form: CREAM
Manufacturer: Guangzhou Yanxi Biotechnology Co., Ltd
Category: otc | Type: HUMAN OTC DRUG LABEL
Date: 20240604

ACTIVE INGREDIENTS: MINERAL OIL 3 mg/50 g; HYDROGENATED AVOCADO OIL 2 mg/50 g
INACTIVE INGREDIENTS: WATER

ACTIVE INGREDIENT

aqua

Keep out of reach of children.

PURPOSE

Moisturizing dry cracked skin

Keep out of reach of children.

DOSAGE AND ADMINISTRATION

Apply to affected area twice per day on cleansed skin. Use continuously for 2-3 weeks for best results.

INACTIVE INGREDIENT

aqua

INDICATIONS AND USAGE

Apply to affected area twice per day on cleansed skin. Use continuously for 2-3 weeks for best results.